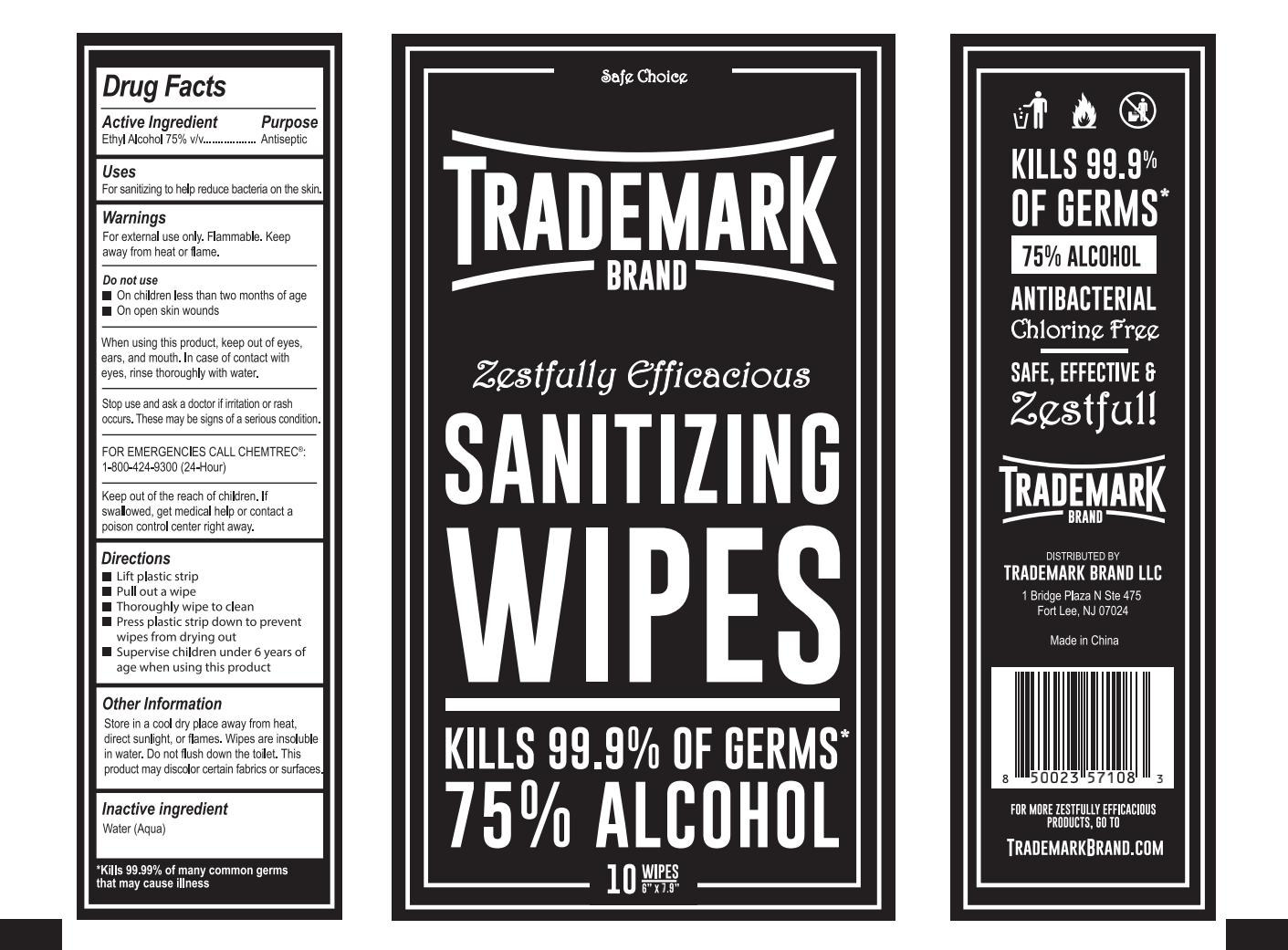 DRUG LABEL: TRADE MARK  SANITIZING  WIPE
NDC: 41546-020 | Form: CLOTH
Manufacturer: Zhejiang Huanghua Biological Technology Co., Ltd
Category: otc | Type: HUMAN OTC DRUG LABEL
Date: 20201211

ACTIVE INGREDIENTS: ALCOHOL 49.85 mL/10 1
INACTIVE INGREDIENTS: WATER

ACTIVE INGREDIENT

Ethyl Alcohol 75%

Purpose

Antiseptic

Uses

For sanitizing to help reduce bacteria on the skin.

WARNINGS

For external use only.Fammable. Keep away from heat or flame.

DO NOT USE

On children less than two months of age
On open skin wounds

When using this product, keep out of eyes,ears, and mouth. ln case of contact with eyes, rinse thoroughly with water.

Stop use and ask a doctor if irritation orrash occurs.These may be signs of a serious condition.

KEEP OUT OF REACH OF CHILDREN

Keep out of the reach of children. lf swallowed, get medical help or contacta poison control center right away.

Directions

Open packet

Pul out wipe
Thoroughly wipe to clean

Discard wipe properly

Discard empty package

Supervise children under 6 years of age when using this product

Other Information

Store in a cool dry place away from heat,direct sunlight,or flames.Wipe is insoluble in water. Do not flush down the toilet. This product may discolor certain fabrics or surfaces.

INACTIVE INGREDIENT

water